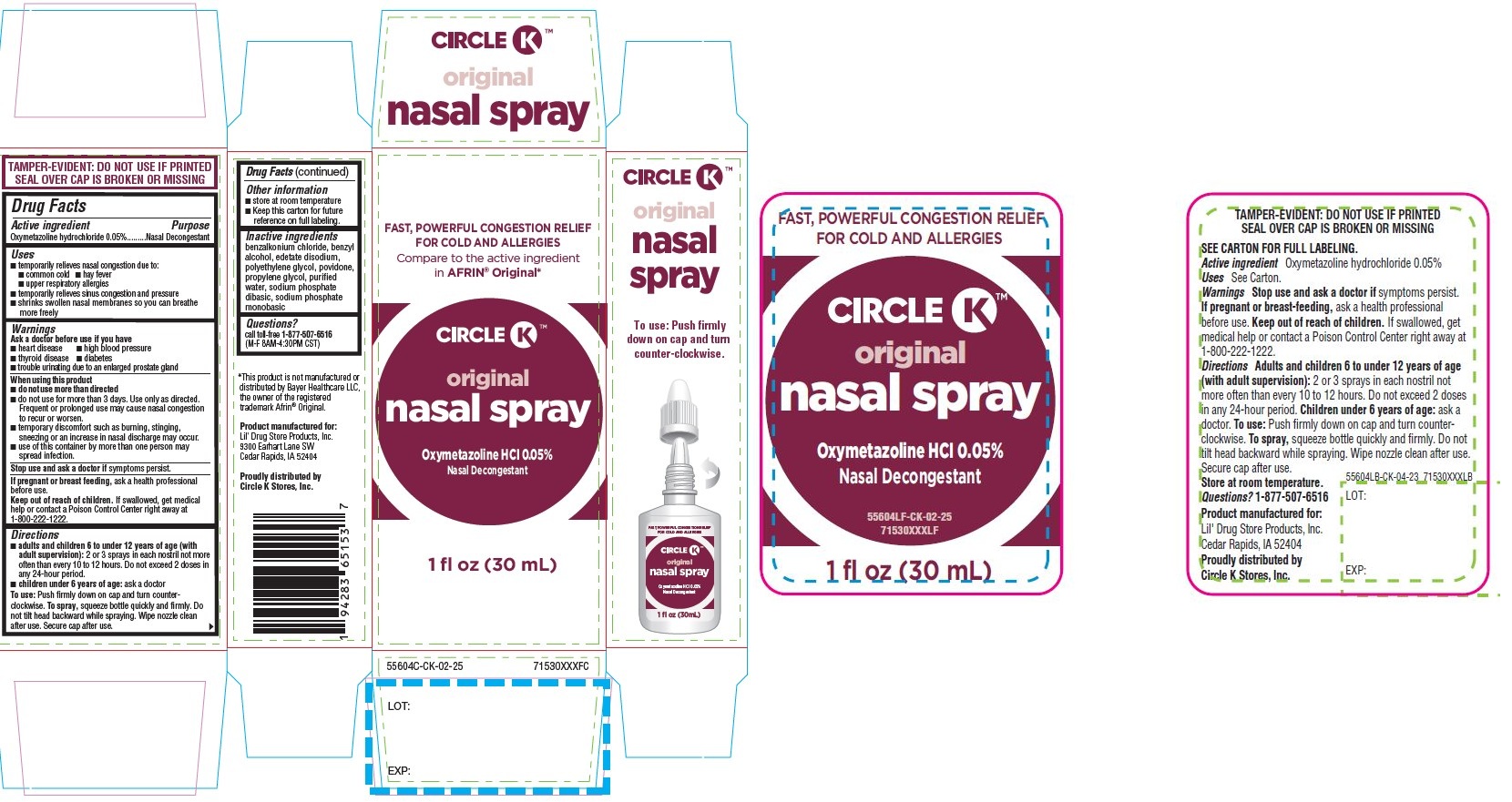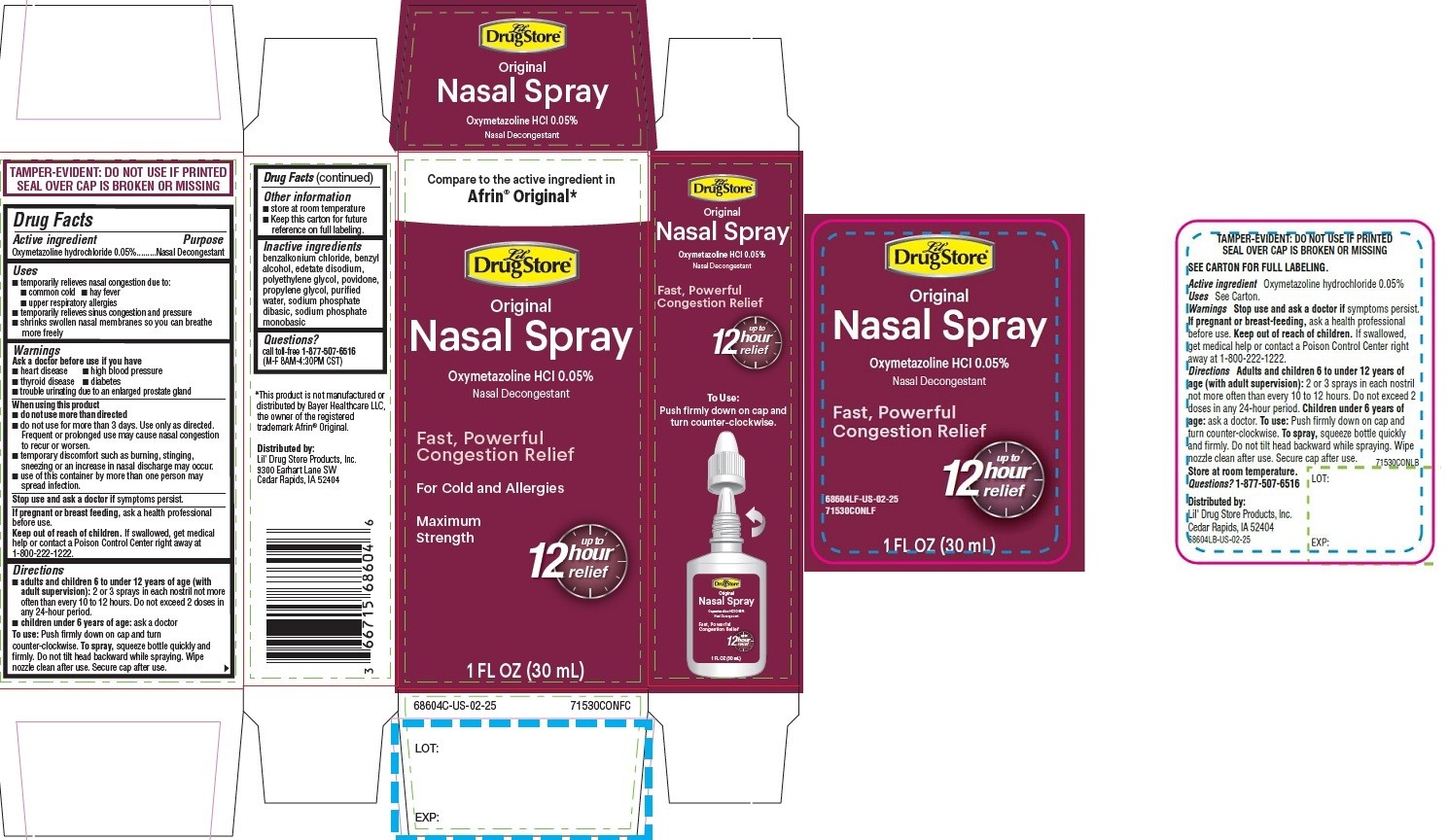 DRUG LABEL: Nasal Spray, Lil Drug Store
NDC: 66715-6760 | Form: SPRAY
Manufacturer: Lil' Drug Store Products, Inc.
Category: otc | Type: HUMAN OTC DRUG LABEL
Date: 20250912

ACTIVE INGREDIENTS: OXYMETAZOLINE HYDROCHLORIDE 0.05 g/100 mL
INACTIVE INGREDIENTS: POLYETHYLENE GLYCOL, UNSPECIFIED; BENZYL ALCOHOL; SODIUM PHOSPHATE, DIBASIC, UNSPECIFIED FORM; BENZALKONIUM CHLORIDE; EDETATE DISODIUM; WATER; POVIDONE, UNSPECIFIED; SODIUM PHOSPHATE, MONOBASIC, UNSPECIFIED FORM; PROPYLENE GLYCOL

Nasal Spray, 1oz

Drug Facts

Active ingredient

Oxymetazoline hydrochloride 0.05%

Purpose

Nasal Decongestant

Uses

- temporarily relieves nasal congestion due to:
- common cold
- hay fever
- upper respiratory allergies
- temporarily relieves sinus congestion and pressure
- shrinks swollen nasal membranes so you can breathe more freely

Warnings

Ask a doctor before use if you have

- heart disease
- high blood pressure
- thyroid disease
- diabetes
- trouble urinating due to an enlarged prostate gland

When using this product

- do not use more than directed
- do not use for more than 3 days. Use only as directed. Frequent or prolonged use may cause nasal congestion to recur or worsen.
- temporary discomfort such as burning, stinging, sneezing or an increase in nasal discharge may occur.
- use of this container by more than one person may spread infection.

Stop use and ask a doctor if symptoms persist.

If pregnant or breast feeding, ask a health professional before use.

Keep out of reach of children. If swallowed, get medical help or contact a Poison Control Center right away at 1-800-222-1222.

Directions

- adults and children 6 to under 12 years of age (with adult supervision): 2 or 3 sprays in each nostril not more often than every 10 to 12 hours. Do not exceed 2 doses in any 24-hour period.
- children under 6 years of age: ask a doctor To use: Push firmly down on cap and turn counter-clockwise. To spray, squeeze bottle quickly and firmly. Do not tilt head backward while spraying. Wipe nozzle clean after use. Secure cap after use.

Other information

- store at room temperature
- Keep this carton for future reference on full labeling.

Inactive ingredients

benzalkonium chloride, benzyl alcohol, edetate disodium, polyethylene glycol, povidone, propylene glycol, purified water, sodium phosphate dibasic, sodium phosphate monobasic

Questions?

call toll-free 1-877-507-6516
(M-F 8AM-4:30PM CST)

PDP/Package - Lil' Drug Store®

Compare to the active ingredient in
Afrin® Original*

[Lil' Drug Store logo]

Original

Nasal Spray

Oxymetazoline HCl 0.05%

Nasal Decongestant

Fast, Powerful
Congestion Relief
For Cold and Allergies
Maximum
Strength

up to

12 hour

relief

1 FL OZ (30 mL)

PDP/Package - Circle K™

FAST, POWERFUL CONGESTION RELIEF
FOR COLD AND ALLERGIES
Compare to the active ingredient
in AFRIN® Original*

[Circle K logo)

original
nasal spray
Oxymetazoline HCI 0.05%
Nasal Decongestant

1 fl oz (30 mL)